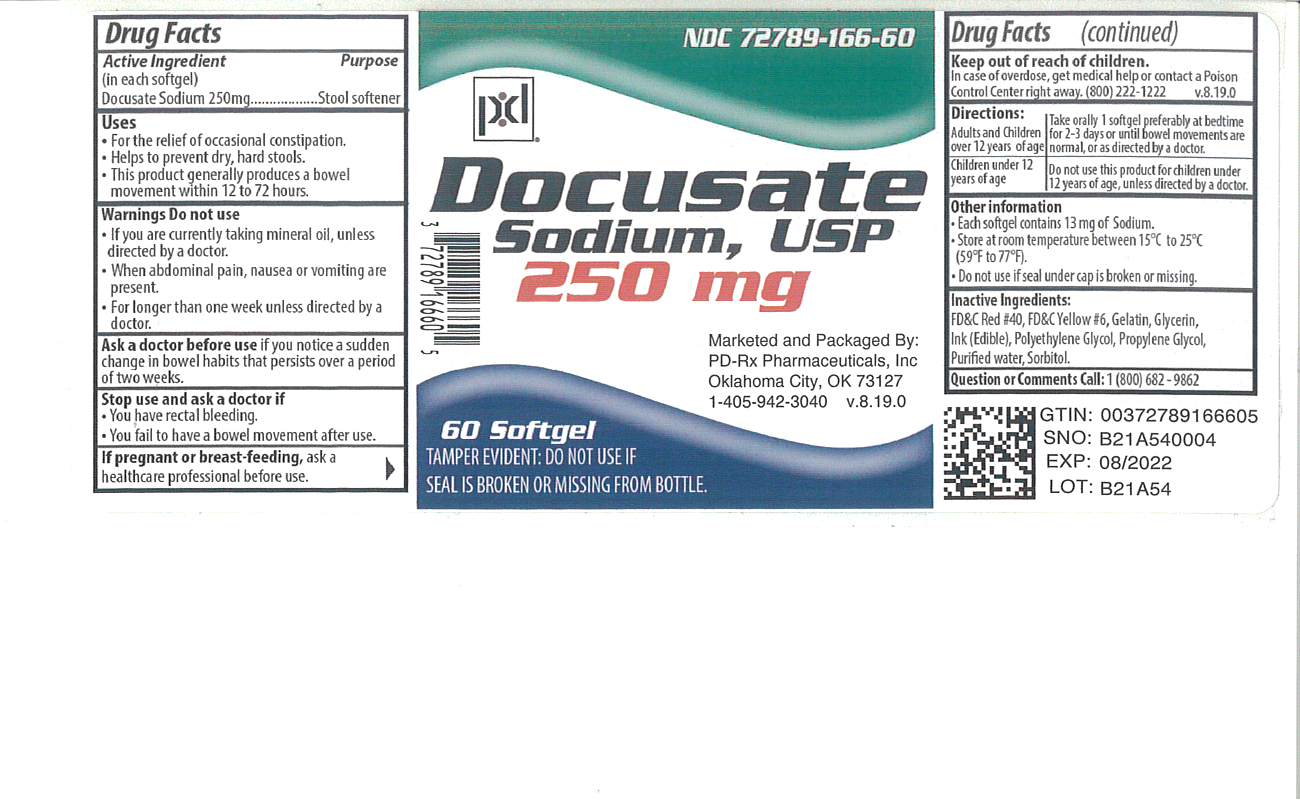 DRUG LABEL: Docusate Sodium
NDC: 72789-166 | Form: CAPSULE, LIQUID FILLED
Manufacturer: PD-Rx Pharmaceuticals, Inc.
Category: otc | Type: HUMAN OTC DRUG LABEL
Date: 20250205

ACTIVE INGREDIENTS: DOCUSATE SODIUM 250 mg/1 1
INACTIVE INGREDIENTS: FD&C RED NO. 40; FD&C YELLOW NO. 6; GELATIN, UNSPECIFIED; GLYCERIN; POLYETHYLENE GLYCOL 1000; PROPYLENE GLYCOL; WATER; SORBITOL

Docusate Sodium, USP
Stool Softener

Active Ingredient (in each softgel)

Docusate Sodium 250 mg

Purpose

Stool Softener

Uses

- For the relief of occasional constipation.
- Helps to prevent dry, hard stools.
- This product generally produces a bowel movement within 12 to 72 hours.

WARNINGS Do not use:

- If you are currently taking mineral oil, unless directed by a doctor.
- When abdominal pain, nausea, or vomiting are present.
- For longer than one week unless directed by a doctor.

Ask a doctor before use

if you notice a sudden change in bowel habits that persists over a period of two weeks.

Stop use and ask a doctor

if you have rectal bleeding or you fail to have a bowel movement after use.

If pregnant or breast-feeding,

ask a healthcare professional before use.

Keep out of reach of children.

In case of overdose, get medical help or contact a Poison Control Center right away (800) 222-1222.

Directions

Adults and Children over 12 years of age | Take orally 1 softgel preferably at bedtime for 2-3 days or until bowel movements are normal, or as directed by a doctor.
Children under 12 years of age | Do not use this product for children under 12 years of age, unless directed by a doctor.

Other Information

- Each softgel contains 13 mg of Sodium.
- Store at room temperature between 15°C to 30°C (59°F to 86°F).
- Do not use if printed seal under cap is broken or missing.
- For identification purposes, each softgel will have an imprint that reads NV12.

Inactive Ingredients

FD&C Red #40, FD&C Yellow #6, Gelatin, Glycerin, Ink (Edible), Polyethylene Glycol, Propylene Glycol, Purified Water, Sorbitol.

Questions

Call 1 (800) 682-9862

Package/Label Principal Display Panel

Docusate Sodium, USP
Stool Softener
250 mg Each